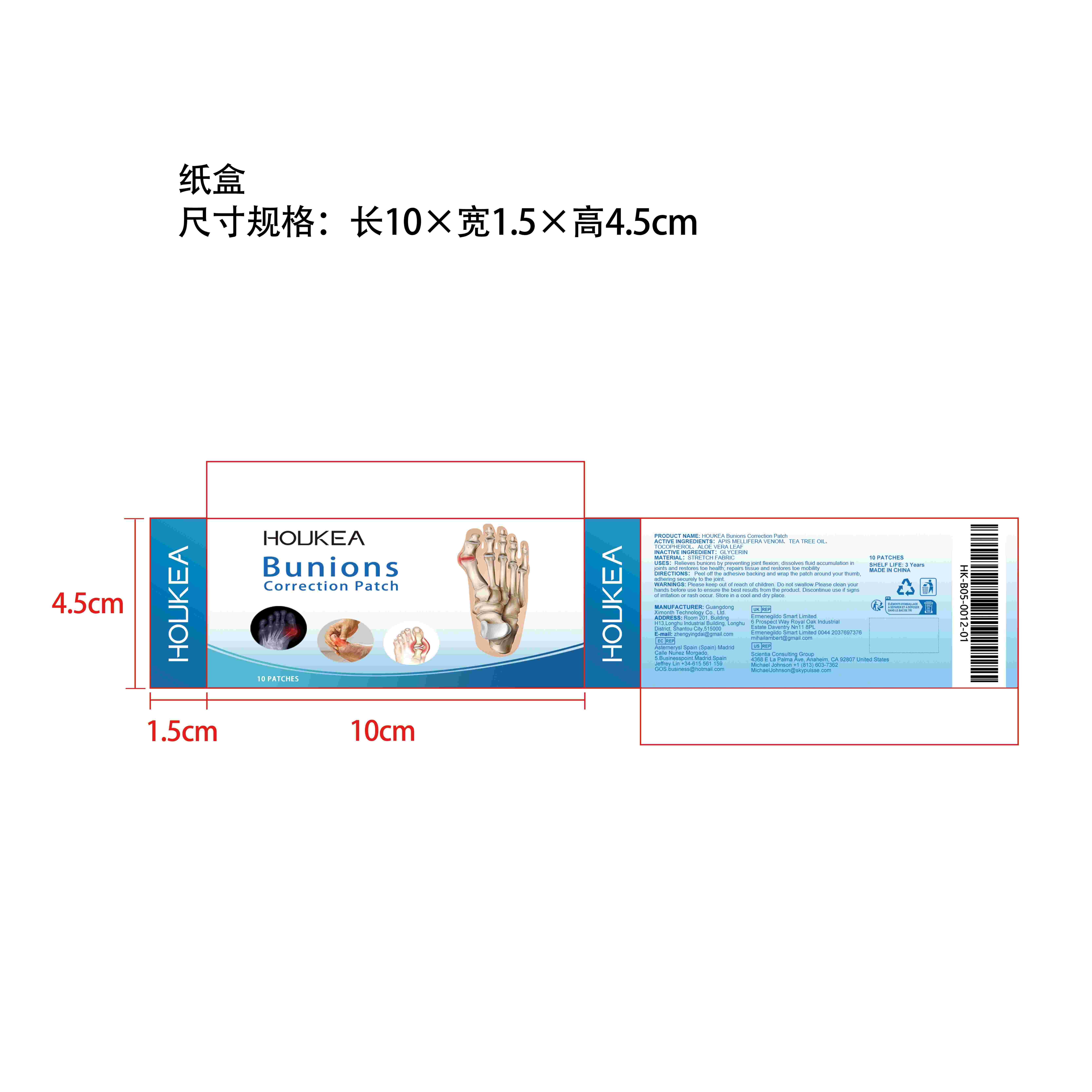 DRUG LABEL: HOUKEA Bunions Correction Patch
NDC: 84660-084 | Form: PATCH
Manufacturer: Guangdong Ximonth Technology Co., Ltd.
Category: otc | Type: HUMAN OTC DRUG LABEL
Date: 20241022

ACTIVE INGREDIENTS: APIS MELLIFERA VENOM 2.5 g/10 g; TEA TREE OIL 2 g/10 g; TOCOPHEROL 1.5 g/10 g; ALOE VERA LEAF 1 g/10 g
INACTIVE INGREDIENTS: GLYCERIN 3 g/10 g

Active Ingredient(s)

APIS MELLIFERA VENOM、TEA TREE OIL、TOCOPHEROL、ALOE VERA LEAF

Purpose

Relieves bunions by preventing joint flexion; dissolves fluid accumulation in joints and restores toe health; repairs tissue and restores toe mobility

Warnings

Please keep out of reach of children.Do not swallow.Please clean your hands before use to ensure the best results from the product.Discontinue use if signs of irritation or rash occur.Store in a cool and dry place.

Do not use

Discontinue use if signs of irritation or rash occur.

STOP USE

Discontinue use if signs of irritation or rash occur.

KEEP OUT OF REACH OF CHILDREN

Please keep out of reach of children. Do not swallow.

STORAGE AND HANDLING

Store in a cool and dry place.

Use

Peel off the adhesive backing and wrap the patch around your thumb, adhering securely to the joint.

INACTIVE INGREDIENT

GLYCERIN